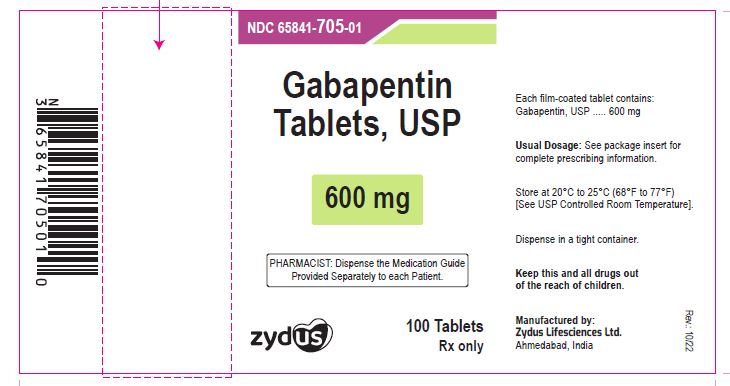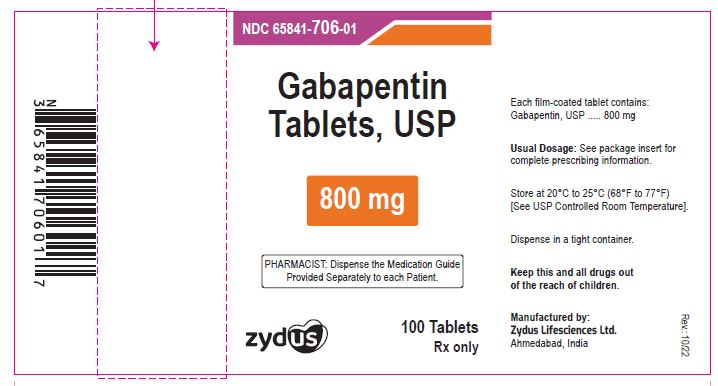 DRUG LABEL: Gabapentin
NDC: 65841-705 | Form: TABLET, FILM COATED
Manufacturer: Zydus Lifesciences Limited
Category: prescription | Type: HUMAN PRESCRIPTION DRUG LABEL
Date: 20241130

ACTIVE INGREDIENTS: GABAPENTIN 600 mg/1 1
INACTIVE INGREDIENTS: COPOVIDONE K25-31; HYDROXYPROPYL CELLULOSE, LOW SUBSTITUTED; MAGNESIUM STEARATE; MANNITOL; POLOXAMER 407; POVIDONE; TALC

GABAPENTIN TABLETS

MEDICATION GUIDE

Manufactured by:

Cadila Heathcare Ltd.

India

PACKAGE LABEL.PRINCIPAL DISPLAY PANEL

NDC 65841-705-01 in bottle of 100 tablets

Gabapentin Tablets USP, 600 mg

Rx only

100 tablets

NDC 65841-706-01 in bottle of 100 tablets

Gabapentin Tablets USP, 800 mg

Rx only

100 tablets